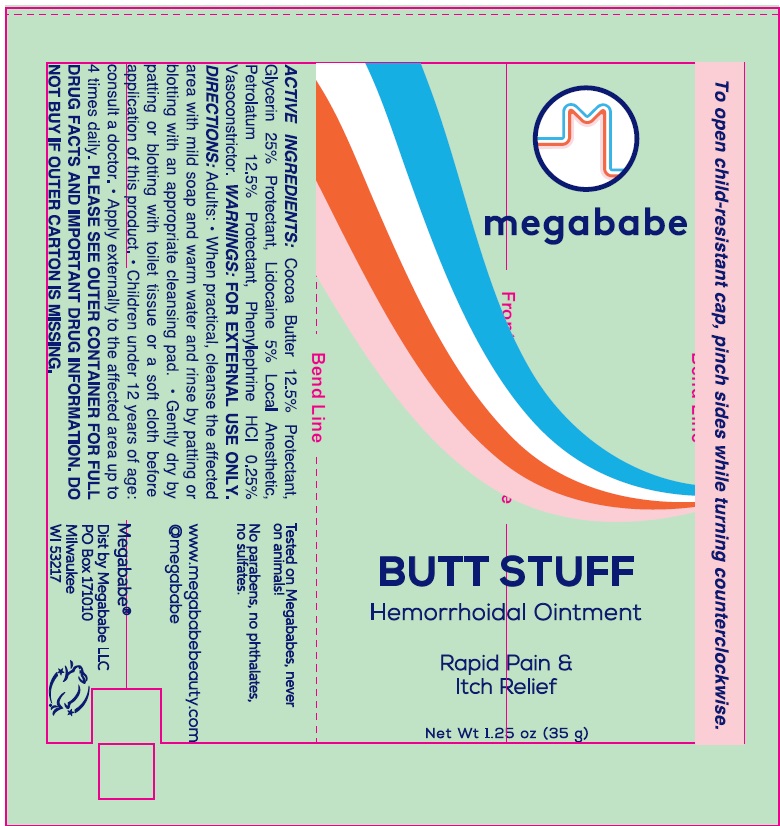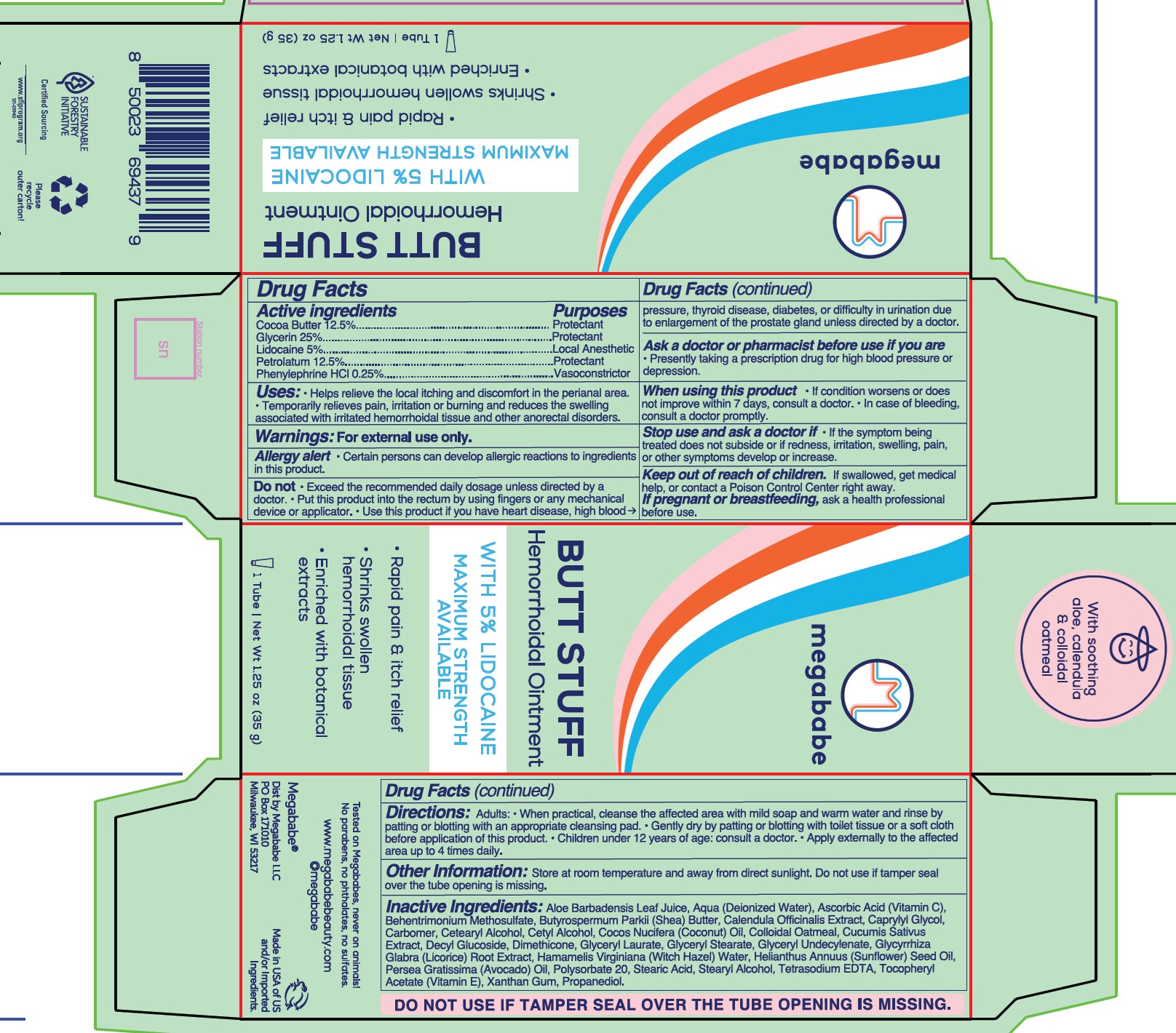 DRUG LABEL: MegaBabe Butt Stuff Hemorrhoidal
NDC: 84000-502 | Form: OINTMENT
Manufacturer: MEGABABE, LLC
Category: otc | Type: HUMAN OTC DRUG LABEL
Date: 20240612

ACTIVE INGREDIENTS: COCOA BUTTER 125 mg/1 g; GLYCERIN 250 mg/1 g; LIDOCAINE 50 mg/1 g; PETROLATUM 125 mg/1 g; PHENYLEPHRINE HYDROCHLORIDE 2.5 mg/1 g
INACTIVE INGREDIENTS: ALOE VERA LEAF; WATER; ASCORBIC ACID; BEHENTRIMONIUM METHOSULFATE; SHEA BUTTER; CALENDULA OFFICINALIS FLOWER; CAPRYLYL GLYCOL; CARBOMER HOMOPOLYMER, UNSPECIFIED TYPE; CETOSTEARYL ALCOHOL; COCONUT OIL; OATMEAL; DECYL GLUCOSIDE; DIMETHICONE; GLYCERYL LAURATE; GLYCERYL MONOSTEARATE; GLYCYRRHIZA GLABRA; HAMAMELIS VIRGINIANA TOP WATER; SUNFLOWER OIL; AVOCADO OIL; POLYSORBATE 20; STEARIC ACID; STEARYL ALCOHOL; EDETATE SODIUM; .ALPHA.-TOCOPHEROL ACETATE; XANTHAN GUM; PROPANEDIOL

MegaBabe Butt Stuff Hemorrhoidal Ointment

Active ingredients

Cocoa Butter 12.5%

Glycerin 25%

Lidocaine 5%

Petrolatum 12.5%

Phenylephrine HCL 0.25%

Purposes

Protectant

Local Anesthetic

Vasoconstrictor

Uses:

- Helps relieve the local itching and discomfort in the perianal area.
- Temporarily relieves pain, irritation or burning and reduces the swelling associated with irritated hemorrhoidal tissue and other anorectal disorders.

Warnings:

For external use only.

Allergy alert • Certain persons can develop allergic reactions to ingredients in this product.

Do not

- Exceed the recommended daily dosage unless directed by a doctor.
- Put this product into the rectum by using fingers or any mechanical device or applicator.
- Use this product if you have heart disease, high blood pressure, thyroid disease, diabetes, or difficulty in urination due to enlargement of the prostate gland unless directed by a doctor.

Ask a doctor or pharmacist before use if you are

- Presently taking a prescription drug for high blood pressure or depression.

When using this product

- If condition worsens or does not improve within 7 days, consult a doctor.
- In case of bleeding, consult a doctor promptly.

Stop use and ask a doctor if

- If the symptom being treated does not subside or if redness, irritation, swelling, pain, or other symptoms develop or increase.

Keep out of reach of children.

If swallowed, get medical help, or contact a Poison Control Center right away.

If pregnant or breastfeeding,

ask a health professional before use.

Directions:

Adults: • When practical, cleanse the affected area with mild soap and warm water and rinse by patting or blotting with an appropriate cleansing pad.

- Gently dry by patting or blotting with toilet tissue or a soft cloth before application of this product.
- Children under 12 years of age: consult a doctor.
- Apply externally to the affected area up to 4 times daily.

Other Information:

Store at room temperature and away from direct sunlight. Do not use if tamper seal over the tube opening is missing.

Inactive Ingredients:

Aloe Barbadensis Leaf Juice, Aqua (Deionized Water), Ascorbic Acid (Vitamin C), Behentrimonium Methosulfate, Butyrospermum Parkii (Shea) Butter, Calendula Officinalis Extract, Caprylyl Glycol, Carbomer, Cetearyl Alcohol, Cetyl Alcohol, Cocos Nucifera (Coconut) Oil, Colloidal Oatmeal, Cucumis Sativus Extract, Decyl Glucoside, Dimethicone, Glyceryl Laurate, Glyceryl Stearate, Glyceryl Undecylenate, Glycyrrhiza Glabra (Licorice) Root Extract, Hamamelis Virginiana (Witch Hazel) Water, Helianthus Annuus (Sunflower) Seed Oil, Persea Gratissima (Avocado) Oil, Polysorbate 20, Stearic Acid, Stearyl Alcohol, Tetrasodium EDTA, Tocopheryl Acetate (Vitamin E), Xanthan Gum, Propanediol.